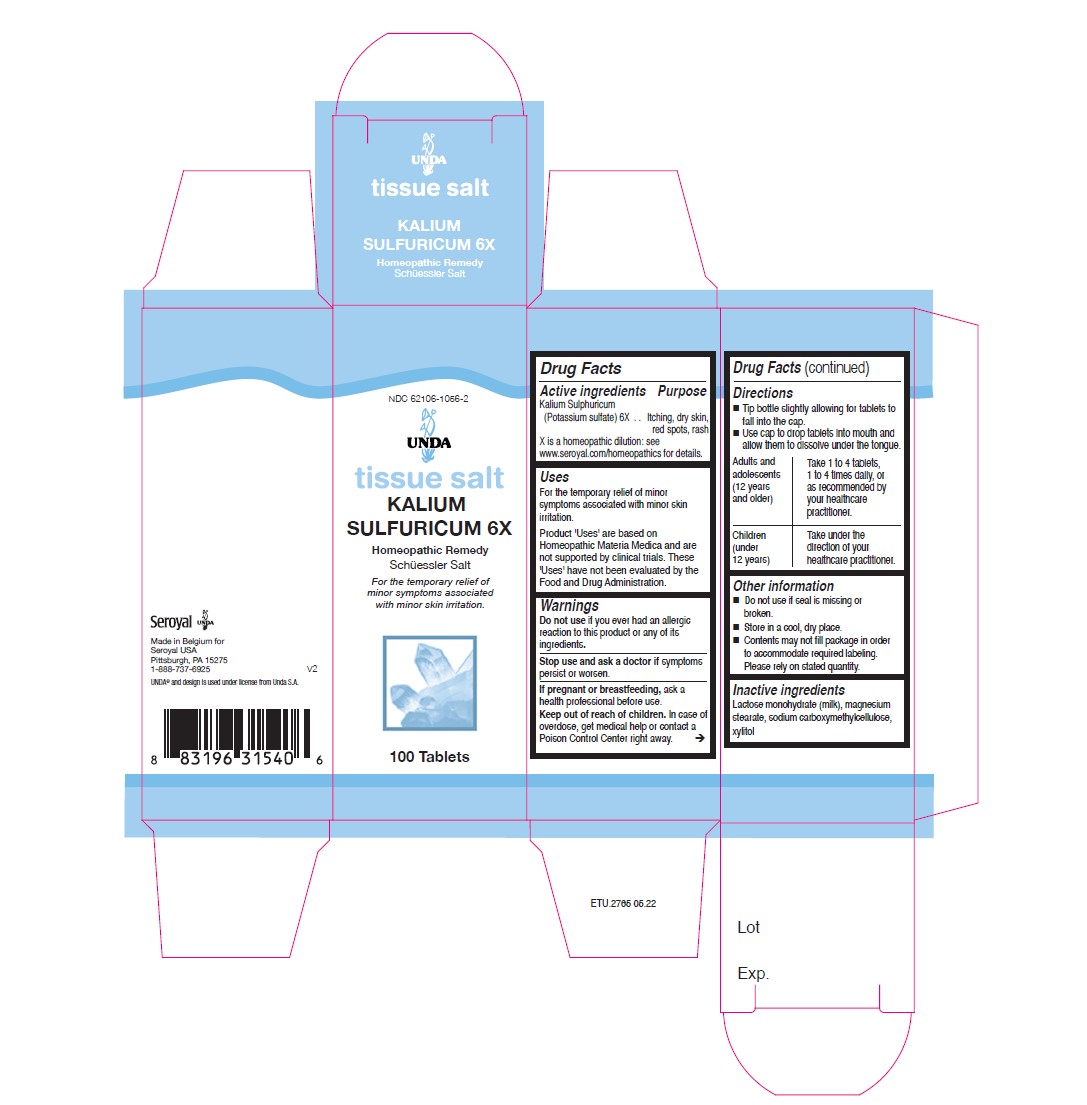 DRUG LABEL: KALIUM SULFURICUM 6X
NDC: 62106-1056 | Form: TABLET
Manufacturer: Seroyal USA
Category: homeopathic | Type: HUMAN OTC DRUG LABEL
Date: 20220707

ACTIVE INGREDIENTS: POTASSIUM SULFATE 6 [hp_X]/1 1
INACTIVE INGREDIENTS: LACTOSE MONOHYDRATE; MAGNESIUM STEARATE; CARBOXYMETHYLCELLULOSE SODIUM; XYLITOL

KALIUM SULFURICUM 6X

Active ingredients
Kalium Sulphuricum (Potassium sulfate) 6X

Uses
For the temporary relief of minor symptoms associated with minor skin irritation.

Warnings
Do not use if you ever had an allergic reaction to this product or any of its ingredients.
Stop use and ask a doctor if symptoms persist or worsen.
If pregnant or breastfeeding, ask a health professional before use.
Keep out of reach of children. In case of overdose, get medical help or contact a
Poison Control Center right away.

PREGNANCY OR BREAST FEEDING

If pregnant or breastfeeding, ask a health professional before use.

Keep out of reach of children. In case of overdose, get medical help or contact a
Poison Control Center right away.

Stop use and ask a doctor if symptoms persist or worsen.

Other information
Do not use if seal is missing or broken.
Store in a cool, dry place.

Inactive ingredients
Lactose monohydrate (milk), magnesium stearate, sodium carboxymethylcellulose, xylitol

Directions
Tip bottle slightly allowing for tablets to fall into the cap.
Use cap to drop tablets into mouth and allow them to dissolve under the tongue.
Adults and adolescents (12 years and older)

Take 1 to 4 tablets, one to four times daily, or as recommended by your healthcare practitioner.

Children (under 12 years)

Take under the direction of your healthcare practitioner.

Uses
For the temporary relief of minor symptoms associated with minor skin irritation.

Directions
Tip bottle slightly allowing for tablets to fall into the cap.
Use cap to drop tablets into mouth and allow them to dissolve under the tongue.
Adults and adolescents (12 years and older)

Take 1 to 4 tablets, one to four times daily, or as recommended by your healthcare practitioner.

Children (under 12 years)

Take under the direction of your healthcare practitioner.

PACKAGE LABEL

UNDA

tissue salt

KALIUM SULFURICUM 6X

Homeopathic Remedy

Schüessler Salt

For the temporary relief of minor symptoms

associated with minor skin irritation.

100 Tablets